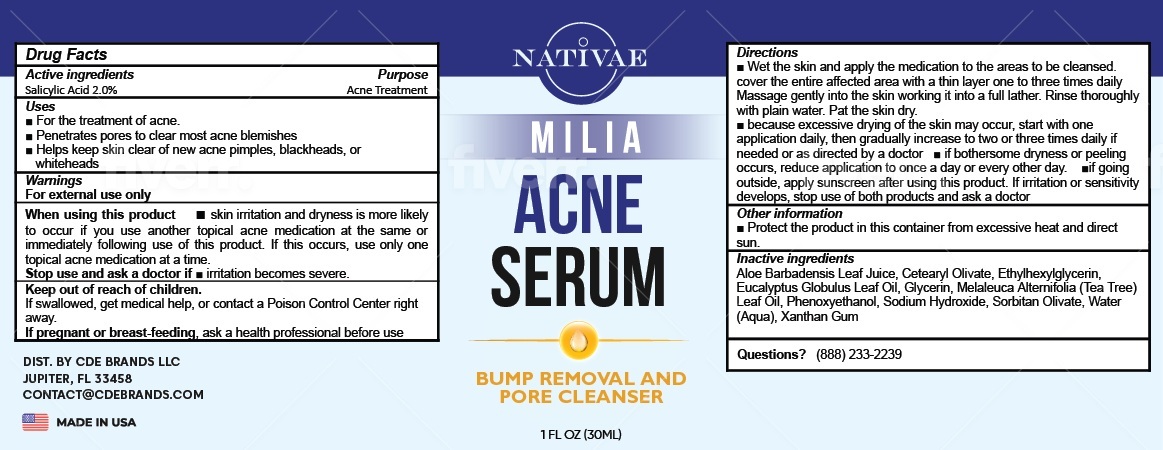 DRUG LABEL: Nativae Milia Acne Serum
NDC: 85065-557 | Form: LIQUID
Manufacturer: CDE BRANDS LLC
Category: otc | Type: HUMAN OTC DRUG LABEL
Date: 20241226

ACTIVE INGREDIENTS: SALICYLIC ACID 20 mg/1 mL
INACTIVE INGREDIENTS: ALOE VERA LEAF; CETEARYL OLIVATE; ETHYLHEXYLGLYCERIN; EUCALYPTUS OIL; GLYCERIN; TEA TREE OIL; PHENOXYETHANOL; SODIUM HYDROXIDE; SORBITAN OLIVATE; WATER; XANTHAN GUM

Nativae Milia Acne Serum

Active ingredients

Salicylic Acid 2.0%

Purpose

Acne Treatment

Uses

- For the treatment of acne.
- Penetrates pores to clear most acne blemishes
- Helps keep skin clear of new acne pimples, blackheads, or whiteheads

Warnings

For external use only

When using this product

- skin irritation and dryness is more likely to occur if you use another topical acne medication at the same or immediately following use of this product. If this occurs, use only one topical acne medication at a time.

Stop use and ask a doctor if

- irritation becomes severe.

Keep out of reach of children.

If swallowed, get medical help, or contact a Poison Control Center right away.

If pregnant or breast-feeding,

ask a health professional before use

Directions

- Wet the skin and apply the medication to the areas to be cleansed. cover the entire affected area with a thin layer one to three times daily. Massage gently into the skin working it into a full lather. Rinse thoroughly with plain water. Pat the skin dry.
- because excessive drying of the skin may occur, start with one application daily, then gradually increase to two or three times daily if needed or as directed by a doctor
- if bothersome dryness or peeling occurs, reduce application to once a day or every other day.
- if going outside, apply sunscreen after using this product. If irritation or sensitivity develops, stop use of both products and ask a doctor

Other information

- Protect the product in this container from excessive heat and direct sun.

Inactive ingredients

Aloe Barbadensis Leaf Juice, Cetearyl Olivate, Ethylhexylglycerin, Eucalyptus Globulus Leaf Oil, Glycerin, Melaleuca Alternifolia (Tea Tree) Leaf Oil, Phenoxyethanol, Sodium Hydroxide, Sorbitan Olivate, Water (Aqua), Xanthan Gum

Questions?

(888) 233-2239